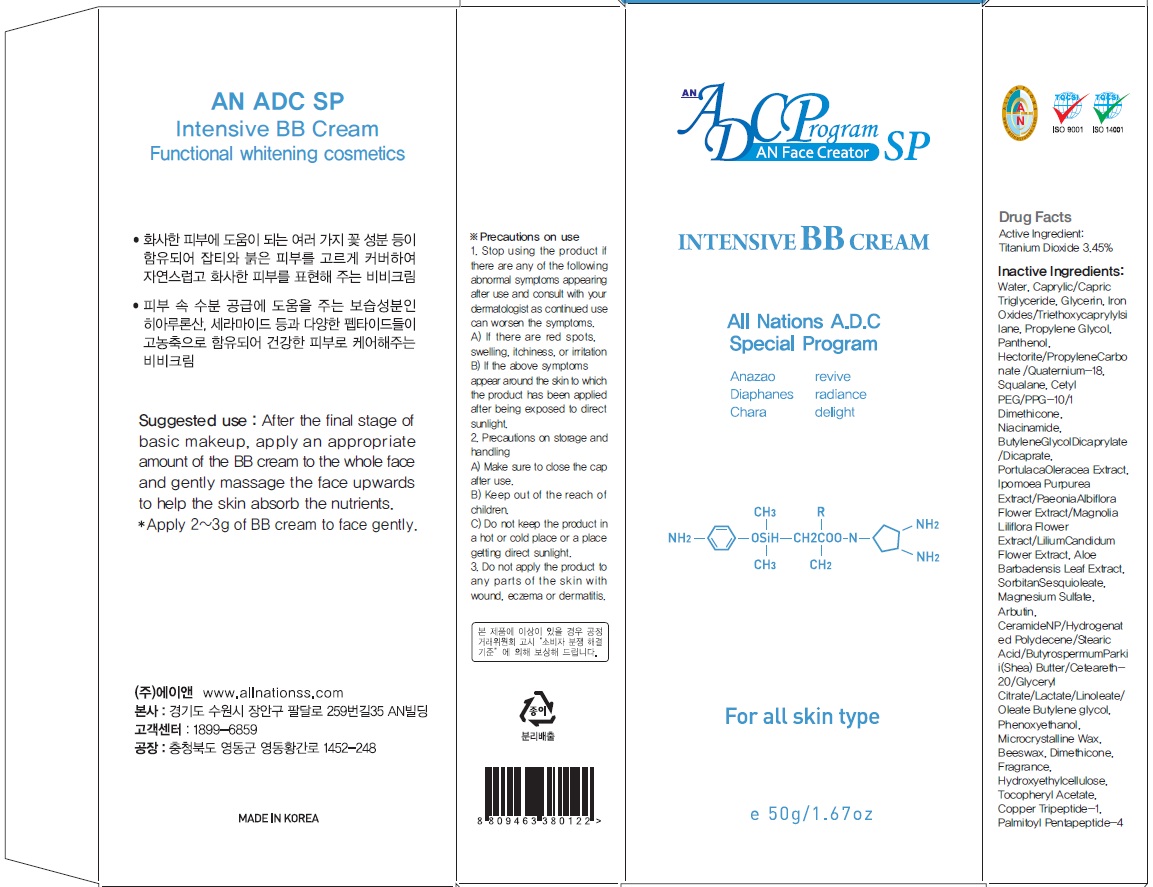 DRUG LABEL: AN ADC SP INTENSIVE BB
NDC: 69153-110 | Form: CREAM
Manufacturer: AN Co Ltd.
Category: otc | Type: HUMAN OTC DRUG LABEL
Date: 20160624

ACTIVE INGREDIENTS: Titanium Dioxide 1.72 g/50 g
INACTIVE INGREDIENTS: Water; Glycerin

ACTIVE INGREDIENT

Active Ingredient: Titanium Dioxide 3.45%

INACTIVE INGREDIENT

Inactive Ingredients: Water, Caprylic/Capric Triglyceride, Glycerin, Iron Oxides/Triethoxycaprylylsilane, Propylene Glycol, Panthenol, Hectorite/PropyleneCarbonate /Quaternium-18, Squalane, Cetyl PEG/PPG-10/1 Dimethicone, Niacinamide, ButyleneGlycol Dicaprylate/Dicaprate, Portulaca Oleracea Extract, Ipomoea Purpurea Extract/Paeonia Albiflora Flower Extract/Magnolia Liliflora Flower Extract/Lilium Candidum Flower Extract, Aloe Barbadensis Leaf Extract, Sorbitan Sesquioleate, Magnesium Sulfate, Arbutin, CeramideNP/Hydrogenated Polydecene/Stearic Acid/ButyrospermumParkii(Shea) Butter/Ceteareth-20/Glyceryl Citrate/Lactate/Linoleate/Oleate Butylene glycol, Phenoxyethanol, Microcrystalline Wax, Beeswax, Dimethicone, Fragrance, Hydroxyethylcellulose, Tocopheryl Acetate, Copper Tripeptide-1, Palmitoyl Pentapeptide-4

PURPOSE

Purpose: Sunscreen

WARNINGS

Precautions on use: 1. Stop using the product if there are any of the following abnormal symptoms appearing after use and consult with your dermatologist as continued use can worsen the symptoms. A) If there are red spots, swelling, itchiness, or irritation B) If the above symptoms appear around the skin to which the product has been applied after being exposed to direct sunlight. 2. Precautions on storage and handling A) Make sure to close the cap after use. B) Keep out of the reach of children. C) Do not keep the product in a hot or cold place or a place getting direct sunlight. 3. Do not apply the product to any parts of the skin with wound, eczema, or dermatitis.

DESCRIPTION

Suggested use: After the final stage of basic makeup, apply an appropriate amount of the BB cream to the whole face and gently massage the face upwards to help the skin absorb the nutrients.

Dosage & administration: Apply 2~3g of BB cream to face gently.